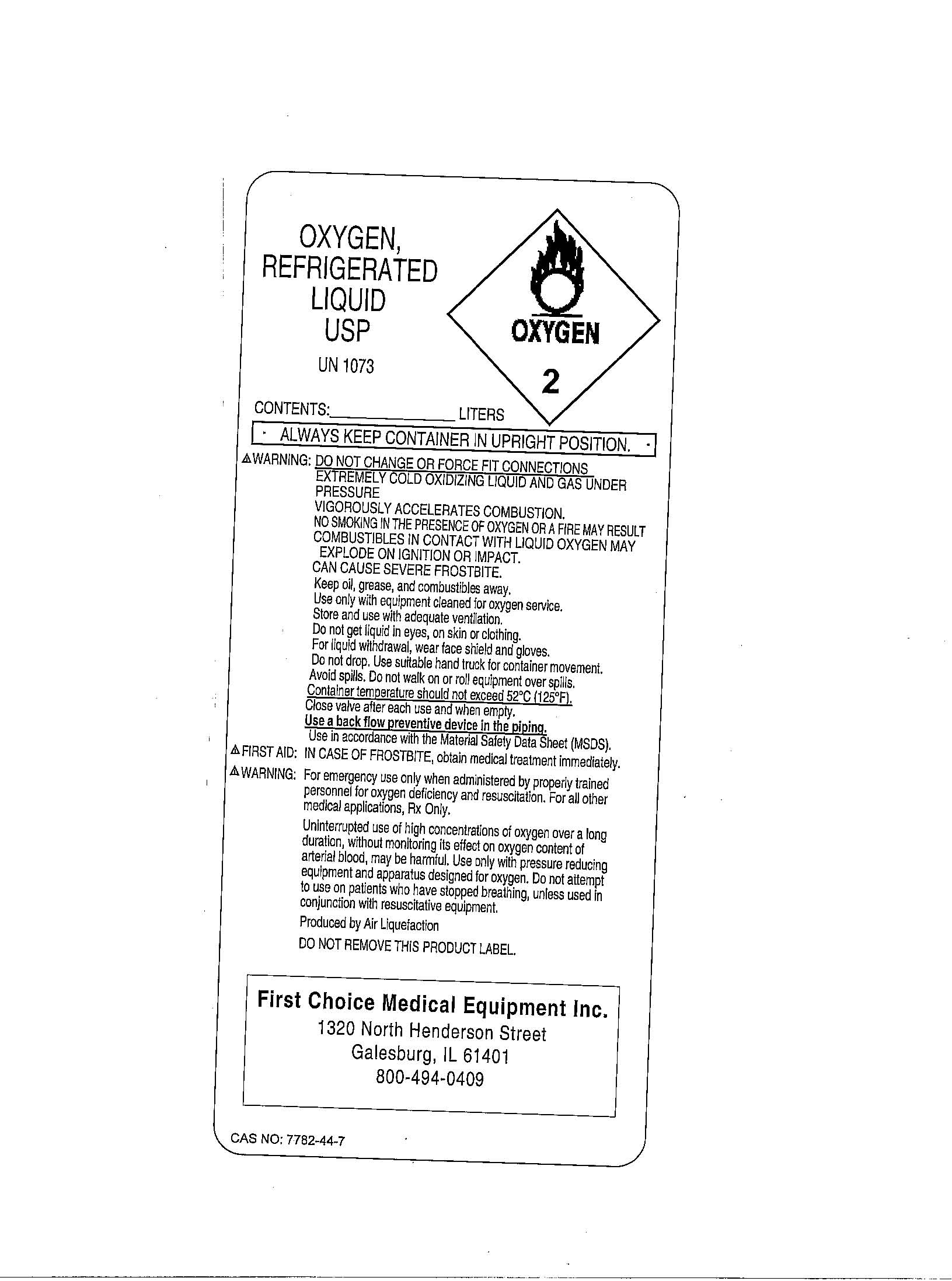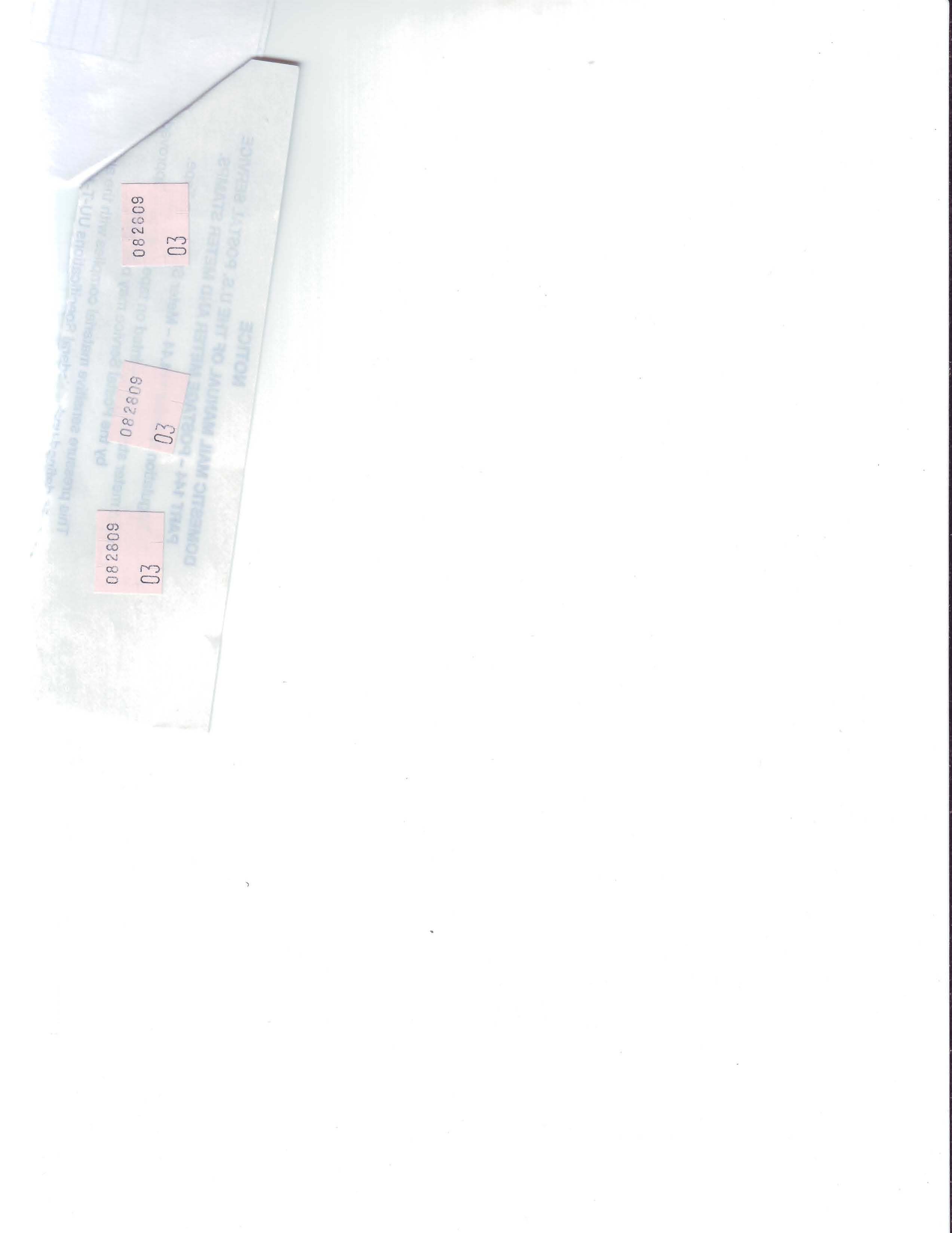 DRUG LABEL: Oxygen
NDC: 15499-1234 | Form: GAS
Manufacturer: First Choice Medical Equipment Inc.
Category: prescription | Type: HUMAN PRESCRIPTION DRUG LABEL
Date: 20090904

ACTIVE INGREDIENTS: Oxygen 99 L/100 L

Oxygen Label